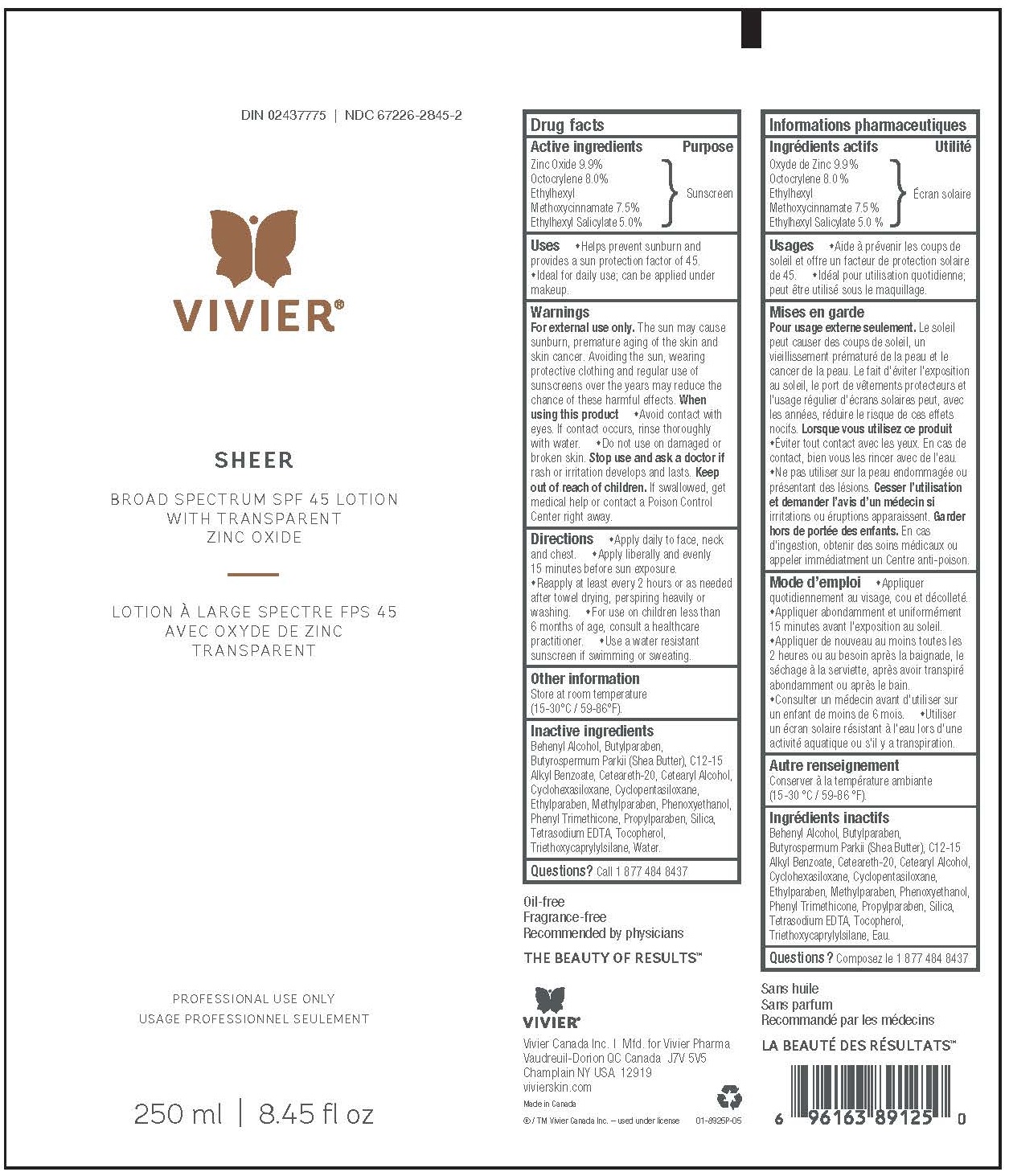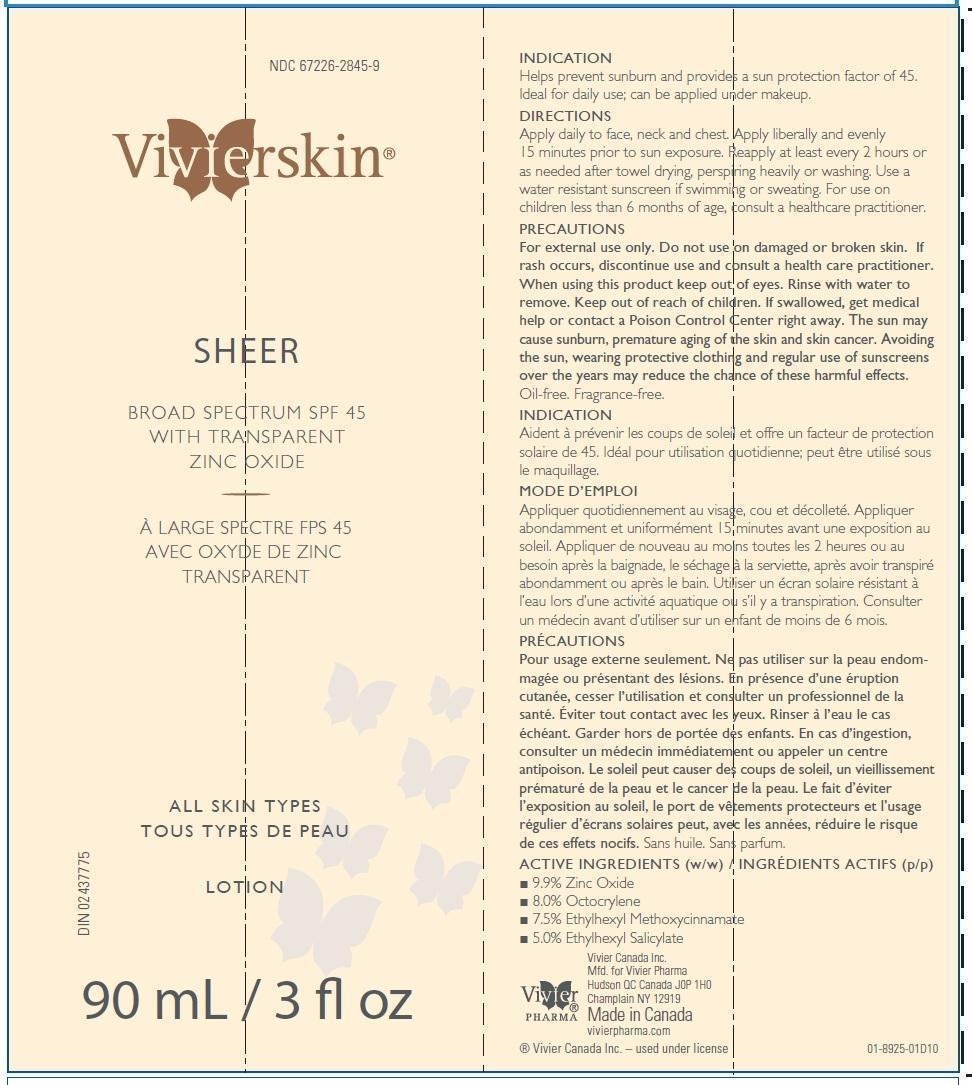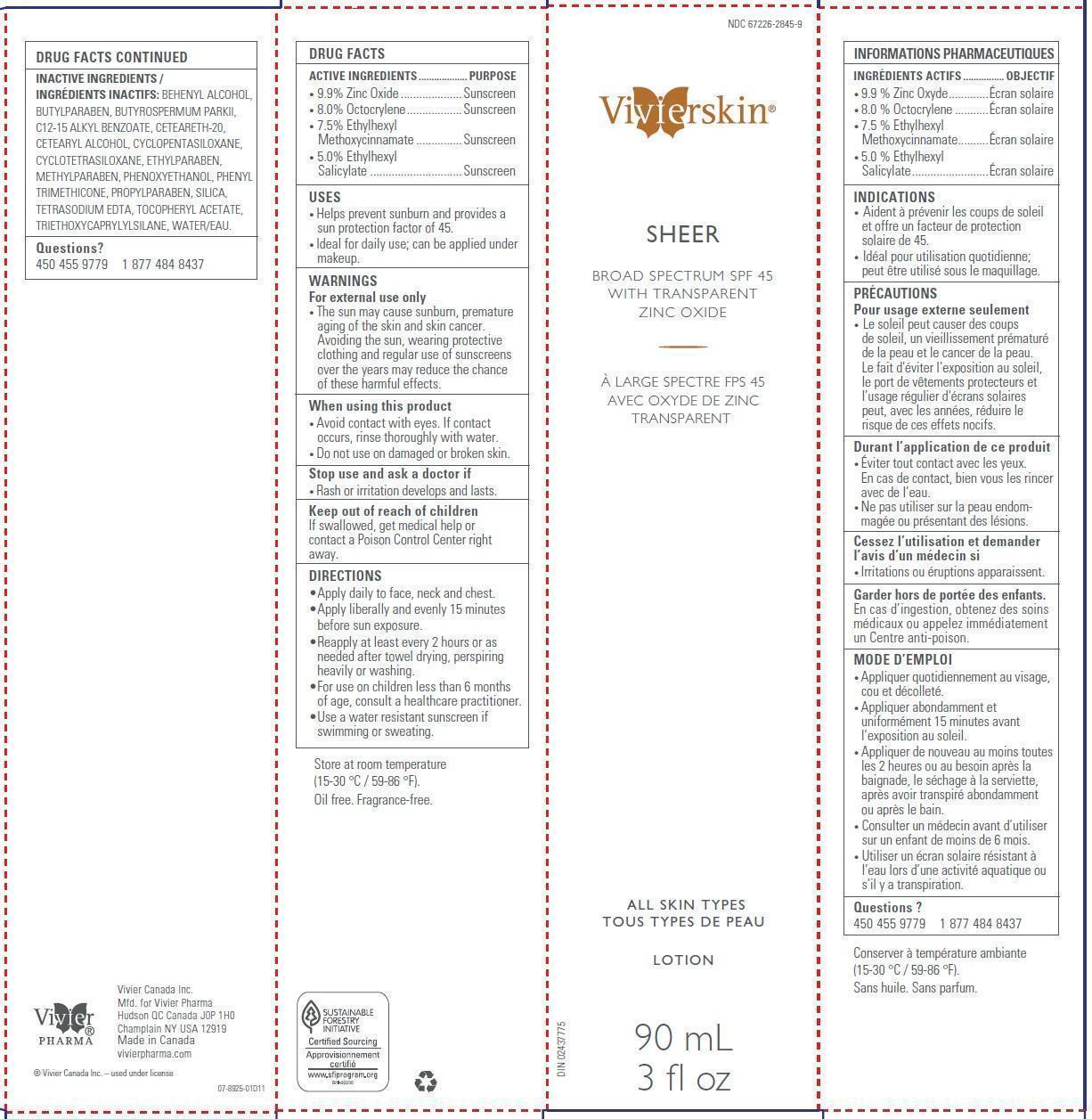 DRUG LABEL: Sheer Broad Spectrum SPF45
NDC: 67226-2845 | Form: LOTION
Manufacturer: Vivier Pharma Inc.
Category: otc | Type: HUMAN OTC DRUG LABEL
Date: 20250404

ACTIVE INGREDIENTS: ZINC OXIDE 99 mg/1 mL; OCTOCRYLENE 80 mg/1 mL; OCTINOXATE 75 mg/1 mL; OCTISALATE 50 mg/1 mL
INACTIVE INGREDIENTS: POLYOXYL 20 CETOSTEARYL ETHER; CETOSTEARYL ALCOHOL; CYCLOMETHICONE 5; CYCLOMETHICONE 4; ETHYLPARABEN; METHYLPARABEN; PHENOXYETHANOL; PHENYL TRIMETHICONE; DOCOSANOL; BUTYLPARABEN; ALKYL (C12-15) BENZOATE; PROPYLPARABEN; SILICON DIOXIDE; EDETATE SODIUM; .ALPHA.-TOCOPHEROL ACETATE; TRIETHOXYCAPRYLYLSILANE; WATER

Sheer Broad Spectrum SPF45

ACTIVE INGREDIENTS

9.9% Zinc Oxide
8.0% Octocrylene
7.5% Ethylhexyl Methoxycinnamate
5.0% Ethylhexyl Salicylate

PURPOSE

Sunscreen

USES

• Helps prevent sunburn and provides a sun protection factor of 45.
• Ideal for daily use; can be applied under makeup.

For external use only

• The sun may cause sunburn, premature aging of the skin and skin cancer. Avoiding the sun, wearing protective clothing and regular use of sunscreens over the years may reduce the chance of these harmful effects.

When using this product

• Avoid contact with eyes. If contact occurs, rinse thoroughly with water.
• Do not use on damaged or broken skin.

Stop use and ask a doctor if

• Rash or irritation develops and lasts.

Keep out of reach of children.

If swallowed, get medical help or contact a Poison Control Center right away.

DIRECTIONS

• Apply daily to face, neck and chest.
• Apply liberally and evenly 15 minutes before sun exposure.
• Reapply at least every 2 hours or as needed after towel drying, perspiring heavily or washing.
• For use on children less than 6 months of age, consult a healthcare practitioner.
• Use a water resistant sunscreen if swimming or sweating.

STORAGE AND HANDLING

Store at room temperature (15-30°C / 59-86°F).

INACTIVE INGREDIENTS

BEHENYL ALCOHOL, BUTYLPARABEN, BUTYROSPERMUM PARKII, C12-15 ALKYL BENZOATE, CETEARETH-20, CETEARYL ALCOHOL, CYCLOPENTASILOXANE, CYCLOTETRASILOXANE, ETHYLPARABEN, METHYLPARABEN, PHENOXYETHANOL, PHENYL TRIMETHICONE, PROPYLPARABEN, SILICA, TETRASODIUM EDTA, TOCOPHERYL ACETATE, TRIETHOXYCAPRYLYLSILANE, WATER/EAU.

Questions?

450 455 9779 1 877 484 8437